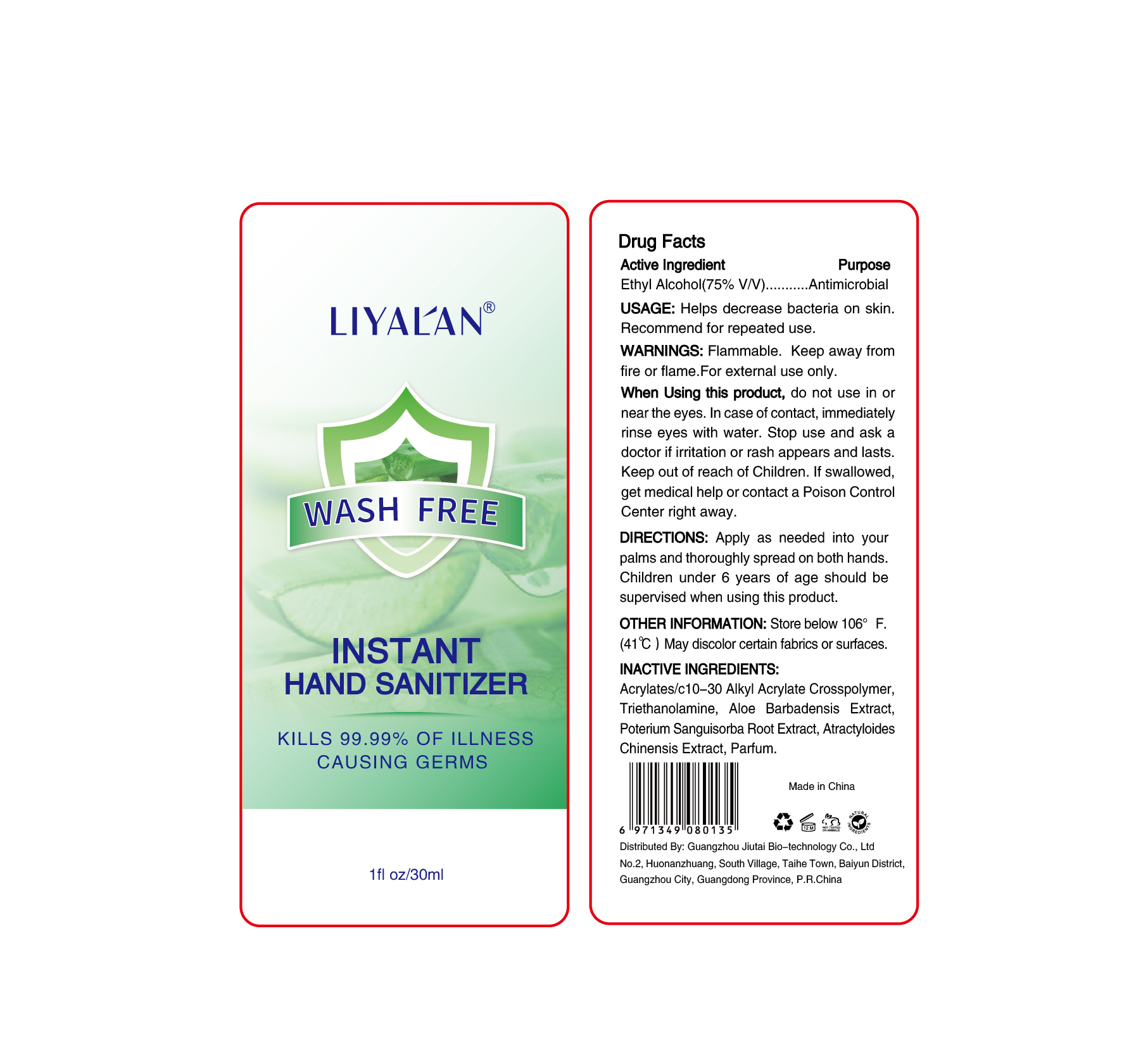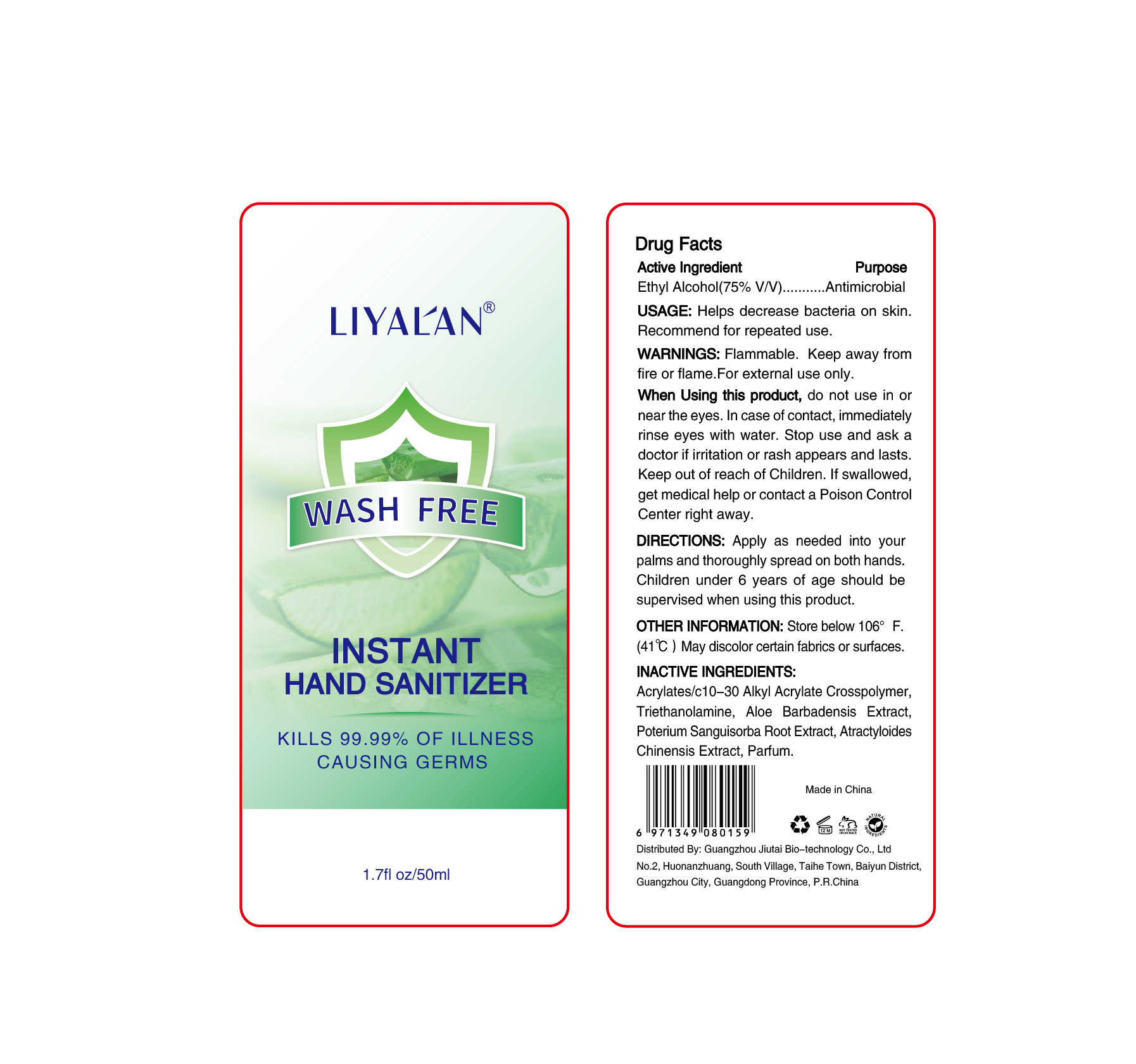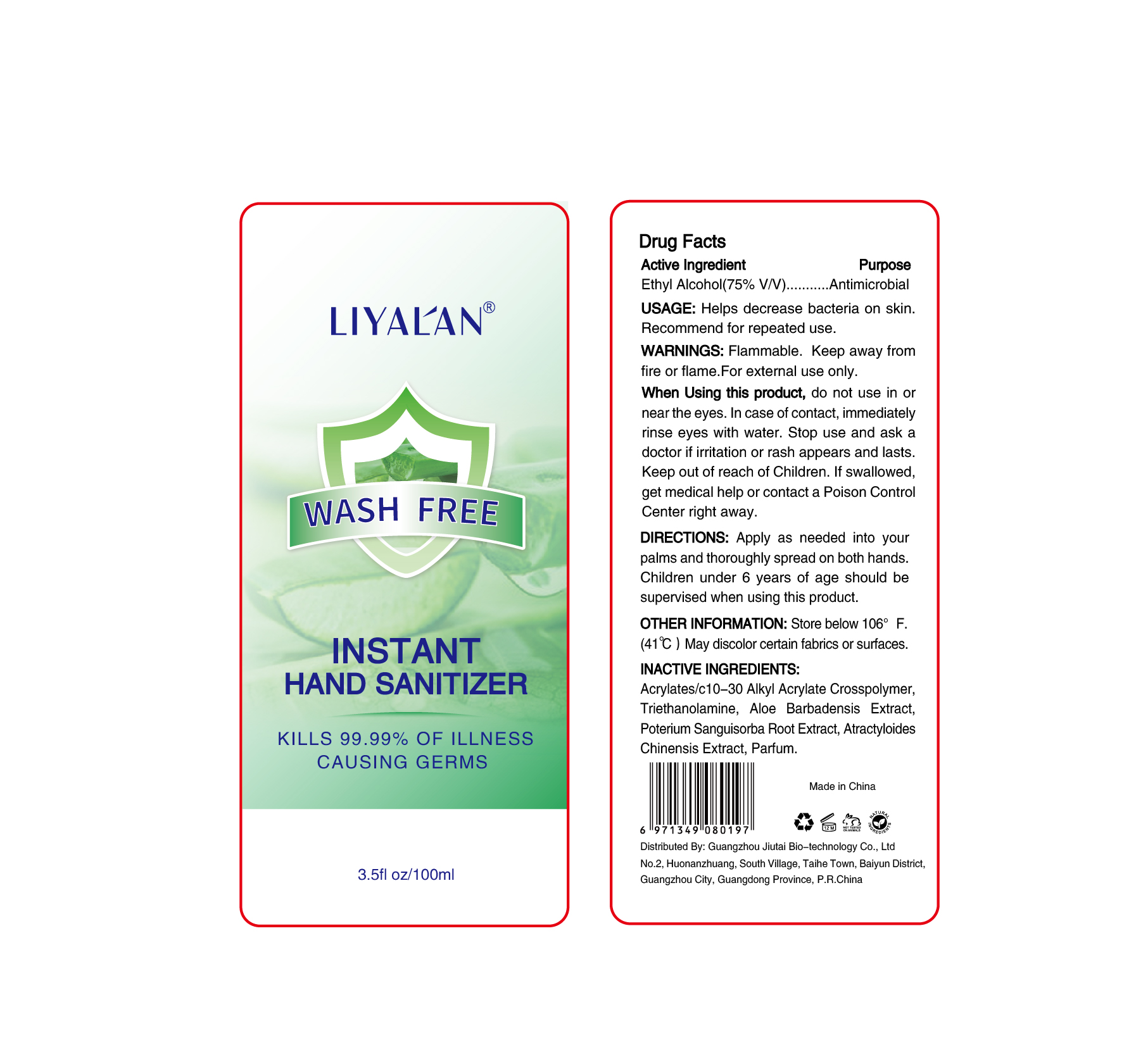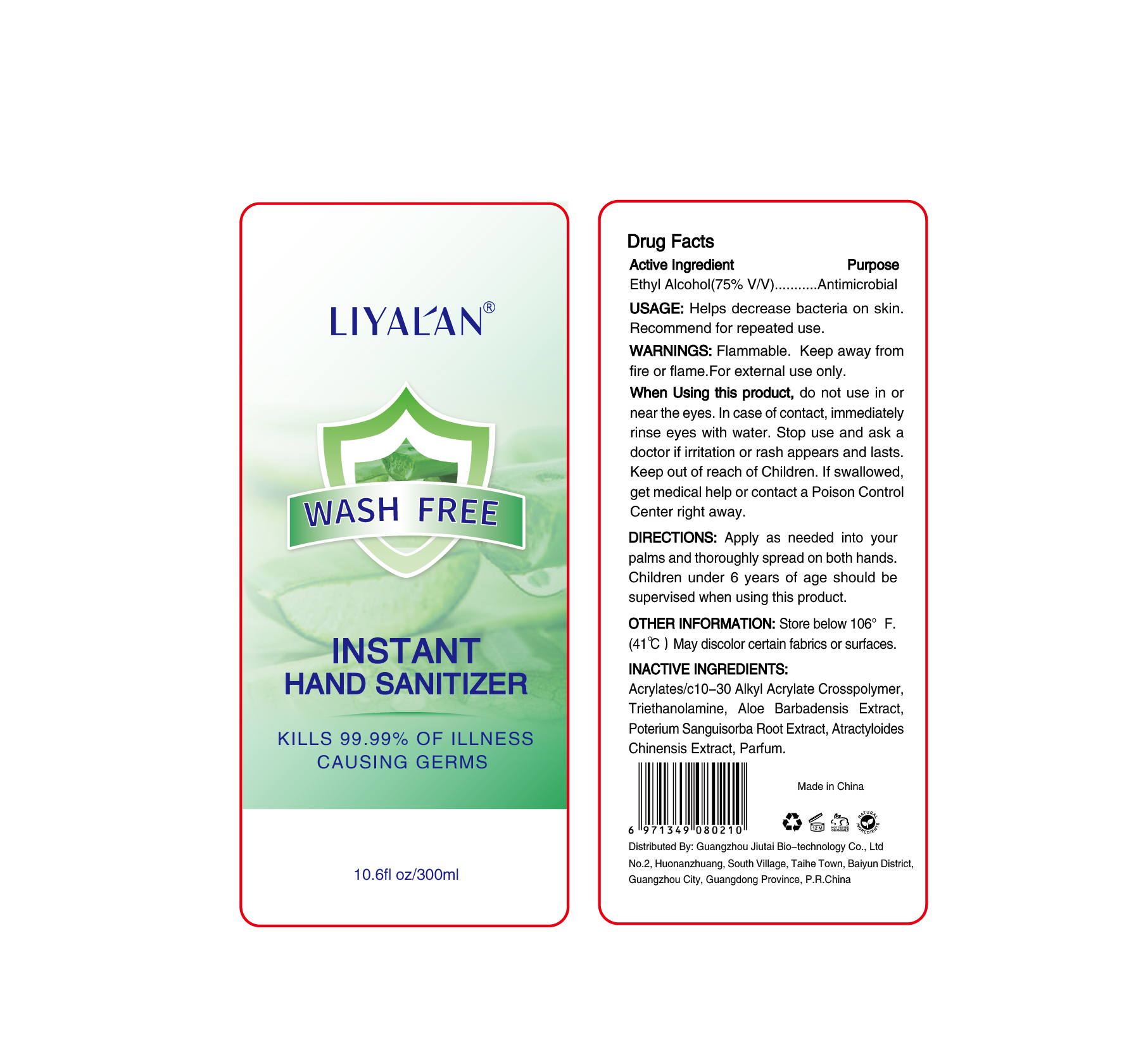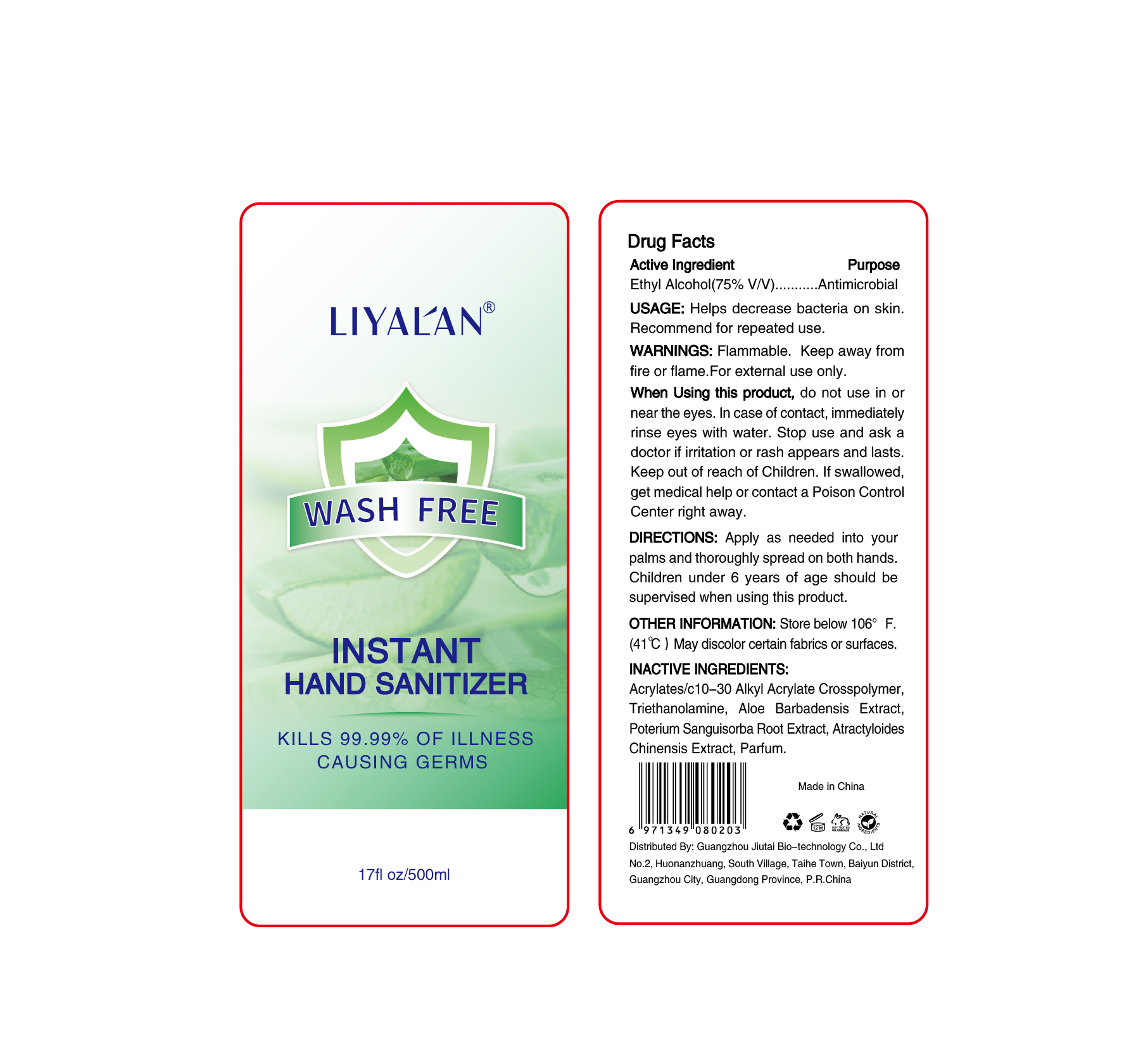 DRUG LABEL: WASH FREE INSTANT  HAND SANITIZER
NDC: 75137-003 | Form: GEL
Manufacturer: Guangzhou JiuTai Bio-technology Co., Ltd.
Category: otc | Type: HUMAN OTC DRUG LABEL
Date: 20200417

ACTIVE INGREDIENTS: ALCOHOL 75 mL/100 mL
INACTIVE INGREDIENTS: CARBOMER INTERPOLYMER TYPE A (ALLYL SUCROSE CROSSLINKED); SANGUISORBA MINOR ROOT; TROLAMINE

绿 WASH FREE INSTANT HAND SANITIZER

Active Ingredient

Ethyl Alcohol(75%V/V)

Purpose

Antimicrobial

USAGE

Helps decrease bacteria on skin.

Recommend for repeated use.

WARNINGS

Flammable.Keep away from fire or flame.For external use only.

When Using this product

do not use in or near the eyes.In case of contact,immediately rinse eyes with water.Stop use and ask a

doctor if irritation or rash appears and lasts.Keep out of reach of Children.If swallowed ,get medical help

or contact a Poison Control Center right away.

DIRECTIONS

Apply as needed into yourpalms and thoroughly spread on both handsChildren under 6 years of age should besupervised when using this product.

OTHER INFORMATION

Store below 106°F.(41℃)

May discolor certain fabrics or surfaces.

INACTIVE INGREDIENTS

Acrylates/c10-30 Alkyl Acrylate Crosspolymer, Triethanolamine, Aloe Barbadensis Extract,
Poterium Sanguisorba Root Extract, Atractyloides Chinensis Extract, Parfum